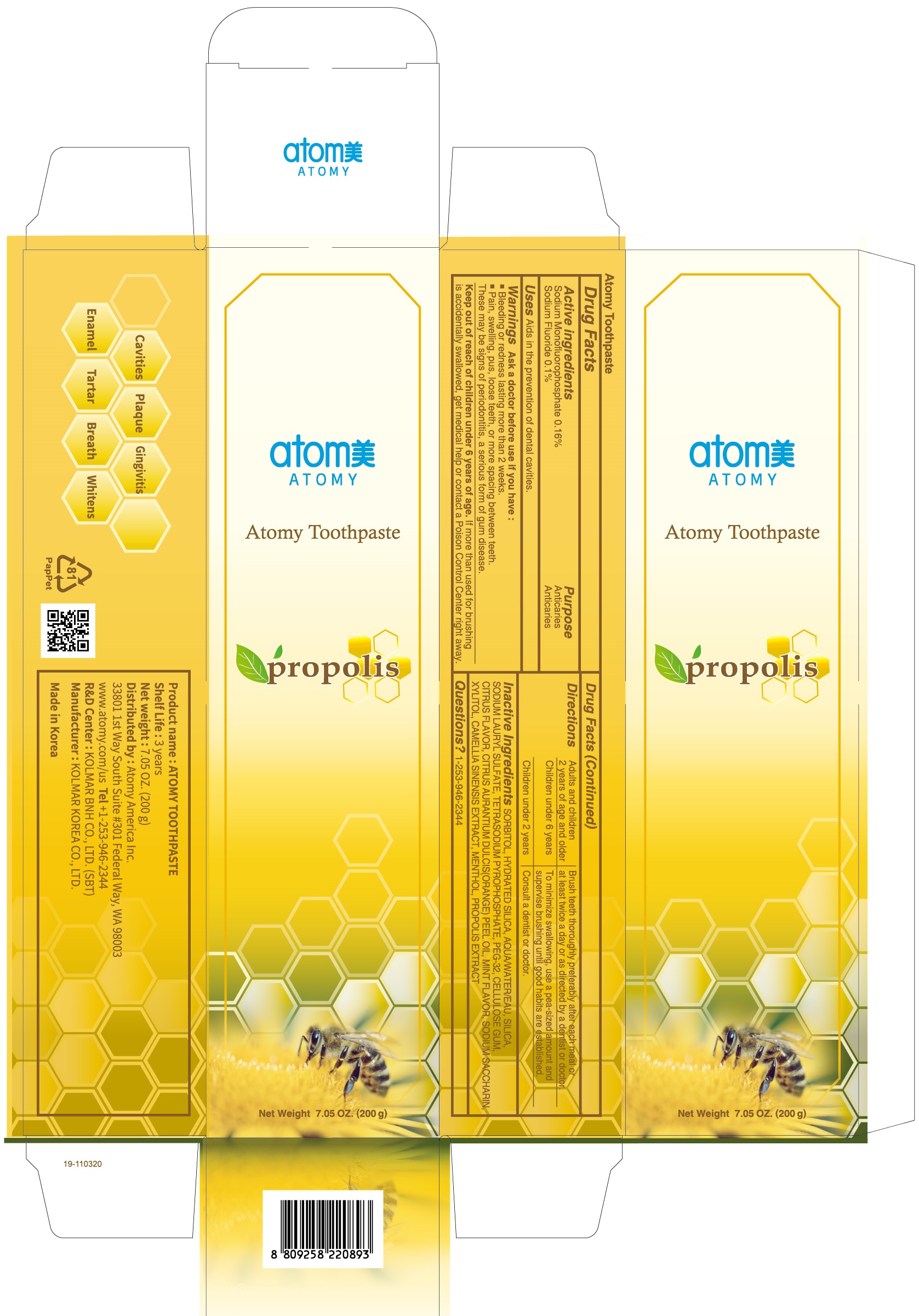 DRUG LABEL: ATOMY PROPOLIS TOOTHPAS TE 200G
NDC: 52257-1370 | Form: PASTE, DENTIFRICE
Manufacturer: ATOMY CO., LTD.
Category: otc | Type: HUMAN OTC DRUG LABEL
Date: 20240130

ACTIVE INGREDIENTS: SODIUM MONOFLUOROPHOSPHATE 0.32 g/200 g; SODIUM FLUORIDE 0.2 g/200 g
INACTIVE INGREDIENTS: SILICON DIOXIDE; SORBITOL; HYDRATED SILICA; WATER; SODIUM LAURYL SULFATE

Active Ingredient: Sodium Monofluorophosphate 0.16%, Sodium Fluoride 0.10%

INACTIVE INGREDIENT

Inactive Ingredients: SORBITOL, HYDRATED SILICA, WATER, SILICA, SODIUM LAURYL SULFATE, TETRASODIUM PYROPHOSPHATE, PEG-32, CELLULOSE GUM, CITRUS FLAVOR, CITRUS AURANTIUM DULCIS(ORANGE) PEEL OIL, MINT FLAVOR, SODIUM SACCHARIN, XYLITOL, CAMELLIA SINENSIS EXTRACT, MENTHOL, PROPOLIS EXTRACT

Purpose: Anticaries

Warnings:

Ask a doctor before use if you have:

Bleeding or redness lasting more than 2 weeks.

Pain, swelling, pus, loose teeth, or more spacing between teeth.

These may be signs of periodontitis, a serious form of gum disease.

Keep out of reach of children under 6 years of age.

If more than used for brushing is accidentally swallowed, get medical help or contact a Poison Control Center right away.

Directions:

1) Adults and children 2 years of age and older: Brush teeth throughly preferably after each meal or at least twice a day or as directed by a dentist or doctor. 2) Children under 6 years: To minimize swallowing, use a pea-sized amount and supervise brushing until good habits are established. 3) Children under 2 years: Consult a dentist or doctor.

Uses:

Aids in the prevention of dental cavities.

Questions?
1-253-946-2344